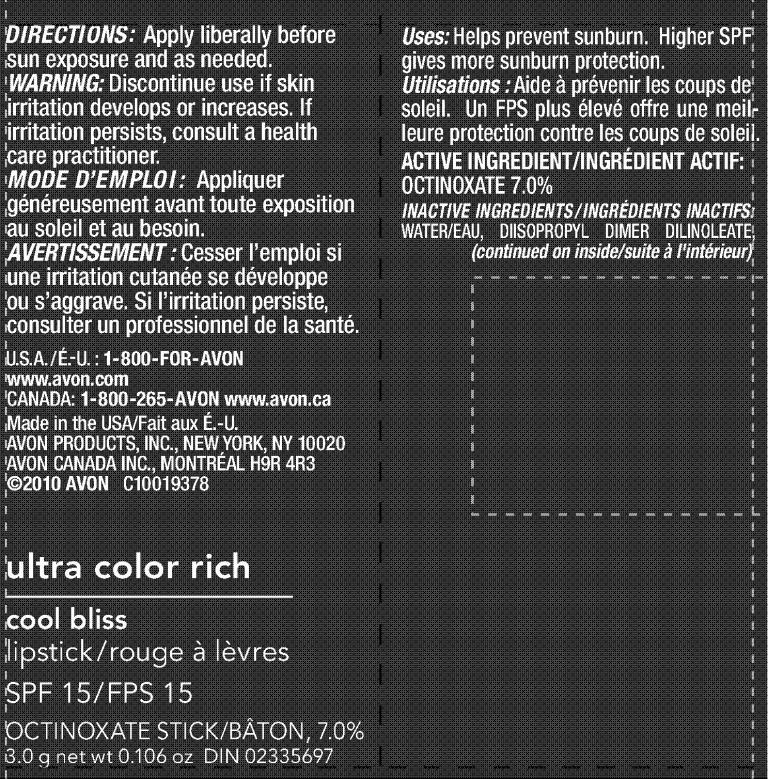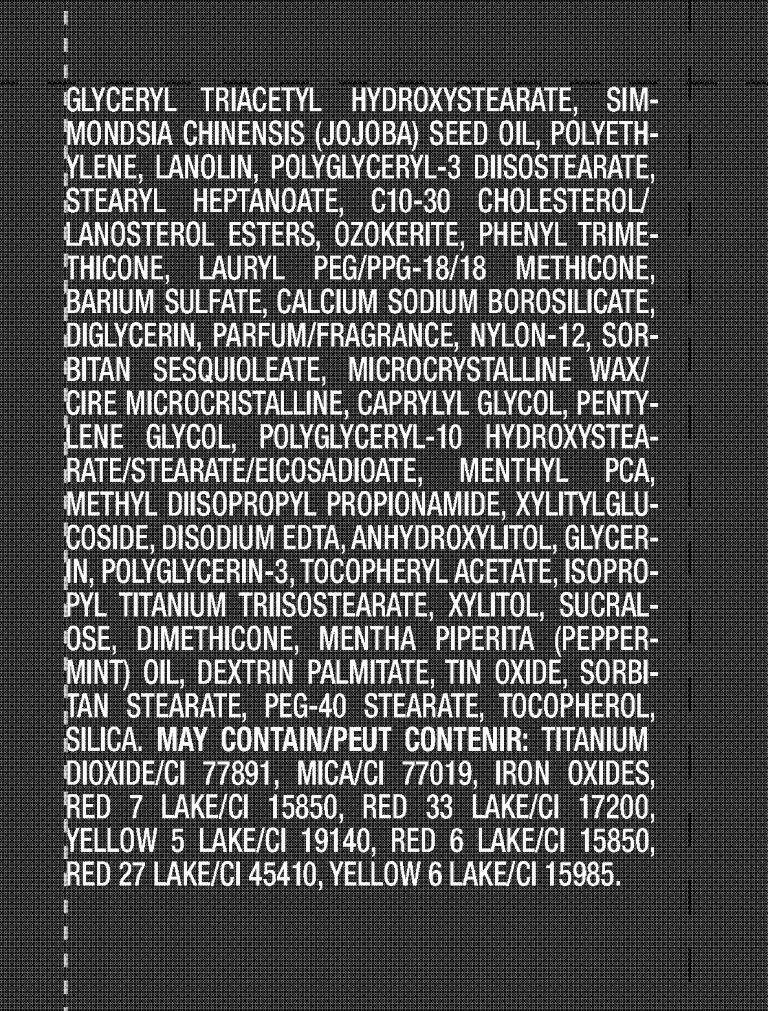 DRUG LABEL: Ultra Color Rich
NDC: 10096-0191 | Form: LIPSTICK
Manufacturer: Avon Products, Inc.
Category: otc | Type: HUMAN OTC DRUG LABEL
Date: 20091229

ACTIVE INGREDIENTS: OCTINOXATE 210 mg/3 g
INACTIVE INGREDIENTS: WATER; LANOLIN; PHENYL TRIMETHICONE; BARIUM SULFATE; SORBITAN SESQUIOLEATE; CAPRYLYL GLYCOL; PENTYLENE GLYCOL; GLYCERIN; XYLITOL; SUCRALOSE; DIMETHICONE; TITANIUM DIOXIDE; MICA

DOSAGE AND ADMINISTRATION

DIRECTIONS: Apply liberally before
sun exposure and as needed.

WARNINGS

WARNING: Discontinue use if skin
irritation develops or increases. If
irritation persists, consult a health
care practitioner.

INDICATIONS AND USAGE

Uses: Helps prevent sunburn. Higher SPF
gives more sunburn protection.

ACTIVE INGREDIENT/INGRÉDIENT ACTIF:
OCTINOXATE 7.0%

INACTIVE INGREDIENTS/ INGRÉDIENTS INACTIFS:
WATER/EAU, DIISOPROPYL DIMER DILINOLEATE,
GLYCERYL TRIACETYL HYDROXYSTEARATE, SIMMONDSIA
CHINENSIS (JOJOBA) SEED OIL, POLYETHYLENE,
LANOLIN, POLYGLYCERYL-3 DIISOSTEARATE,
STEARYL HEPTANOATE, C10-30 CHOLESTEROL/
LANOSTEROL ESTERS, OZOKERITE, PHENYL TRIMETHICONE,
LAURYL PEG/PPG-18/18 METHICONE,
BARIUM SULFATE, CALCIUM SODIUM BOROSILICATE,
DIGLYCERIN, PARFUM/FRAGRANCE, NYLON-12, SORBITAN
SESQUIOLEATE, MICROCRYSTALLINE WAX/
CIRE MICROCRISTALLINE, CAPRYLYL GLYCOL, PENTYLENE
GLYCOL, POLYGLYCERYL-10 HYDROXYSTEARATE/
STEARATE/EICOSADIOATE, MENTHYL PCA,
METHYL DIISOPROPYL PROPIONAMIDE, XYLITYLGLUCOSIDE,
DISODIUM EDTA, ANHYDROXYLITOL, GLYCERIN,
POLYGLYCERIN-3, TOCOPHERYL ACETATE, ISOPROPYL
TITANIUM TRIISOSTEARATE, XYLITOL, SUCRALOSE,
DIMETHICONE, MENTHA PIPERITA (PEPPERMINT)
OIL, DEXTRIN PALMITATE, TIN OXIDE, SORBITAN
STEARATE, PEG-40 STEARATE, TOCOPHEROL,
SILICA. MAY CONTAIN/PEUT CONTENIR: TITANIUM
DIOXIDE/CI 77891, MICA/CI 77019, IRON OXIDES,
RED 7 LAKE/CI 15850, RED 33 LAKE/CI 17200,
YELLOW 5 LAKE/CI 19140, RED 6 LAKE/CI 15850,
RED 27 LAKE/CI 45410, YELLOW 6 LAKE/CI 15985.